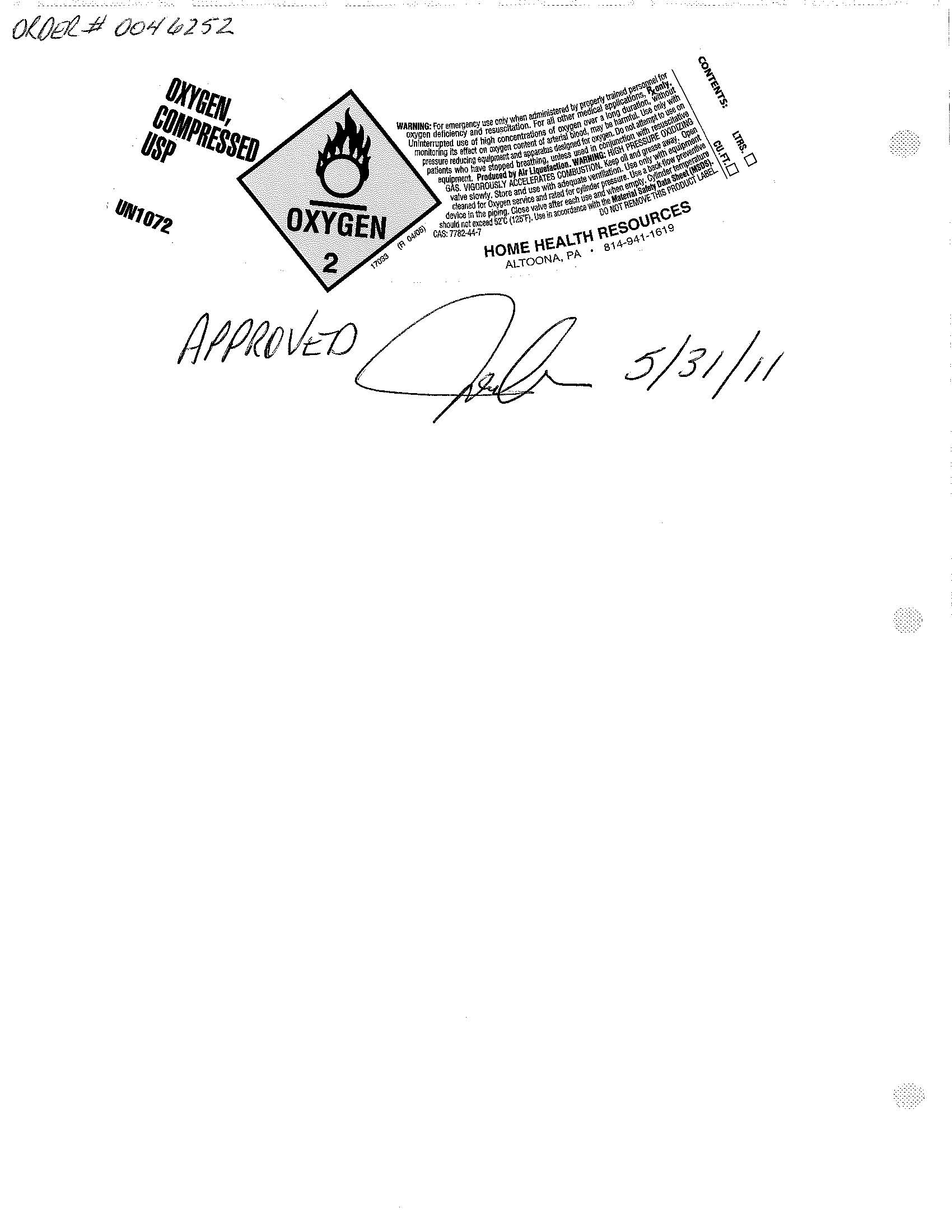 DRUG LABEL: Oxygen
NDC: 64792-0001 | Form: GAS
Manufacturer: Home Health Resource
Category: prescription | Type: HUMAN PRESCRIPTION DRUG LABEL
Date: 20110705

ACTIVE INGREDIENTS: OXYGEN 995 mL/1 L

PACKAGE LABEL

HHR_Compressed_O2.jpg